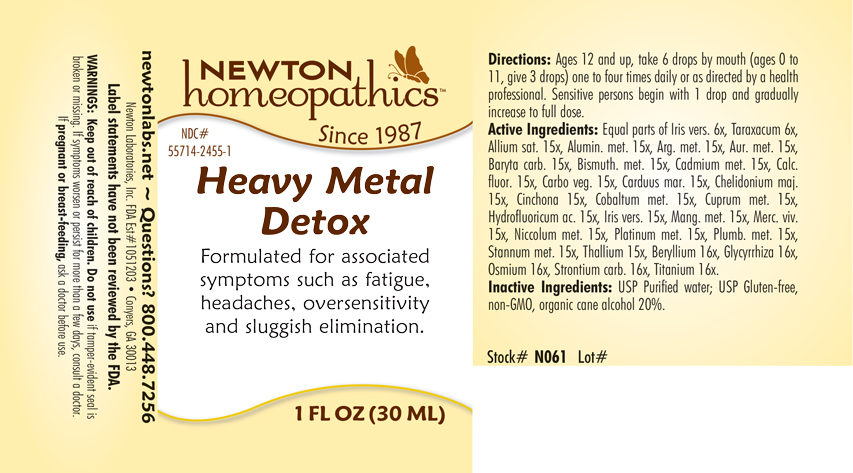 DRUG LABEL: Heavy Metal Detox
NDC: 55714-2455 | Form: LIQUID
Manufacturer: Newton Laboratories, Inc.
Category: homeopathic | Type: HUMAN OTC DRUG LABEL
Date: 20250206

ACTIVE INGREDIENTS: GARLIC 15 [hp_X]/1 mL; ALUMINUM 15 [hp_X]/1 mL; SILVER 15 [hp_X]/1 mL; GOLD 15 [hp_X]/1 mL; BARIUM CARBONATE 15 [hp_X]/1 mL; BERYLLIUM 16 [hp_X]/1 mL; BISMUTH 15 [hp_X]/1 mL; CADMIUM 15 [hp_X]/1 mL; CALCIUM FLUORIDE 15 [hp_X]/1 mL; ACTIVATED CHARCOAL 15 [hp_X]/1 mL; CHELIDONIUM MAJUS 15 [hp_X]/1 mL; CINCHONA OFFICINALIS BARK 15 [hp_X]/1 mL; COBALT 15 [hp_X]/1 mL; COPPER 15 [hp_X]/1 mL; GLYCYRRHIZA GLABRA 16 [hp_X]/1 mL; HYDROFLUORIC ACID 15 [hp_X]/1 mL; IRIS VERSICOLOR ROOT 15 [hp_X]/1 mL; MANGANESE 15 [hp_X]/1 mL; MERCURY 15 [hp_X]/1 mL; NICKEL 15 [hp_X]/1 mL; OSMIUM 16 [hp_X]/1 mL; PLATINUM 15 [hp_X]/1 mL; LEAD 15 [hp_X]/1 mL; TIN 15 [hp_X]/1 mL; STRONTIUM CARBONATE 16 [hp_X]/1 mL; THALLIUM 15 [hp_X]/1 mL; TITANIUM 16 [hp_X]/1 mL; MILK THISTLE 15 [hp_X]/1 mL; TARAXACUM OFFICINALE 6 [hp_X]/1 mL
INACTIVE INGREDIENTS: WATER; ALCOHOL

Heavy 2455L

INDICATIONS & USAGE SECTION

Formulated for associated symptoms such as fatigue, headaches, oversensitivity and sluggish elimination.

DOSAGE & ADMINISTRATION SECTION

Directions: Ages 12 and up, take 6 drops by mouth (ages 0 to 11, give 3 drops) one to four times daily or as directed by a health professional. Sensitive persons begin with 1 drop and gradually increase to full dose.

OTC - ACTIVE INGREDIENT SECTION

Equal parts of Iris versicolor 6x, Taraxacum officinale 6x, Allium sativum 15x, Aluminium metallicum 15x, Argentum metallicum 15x, Aurum metallicum 15x, Baryta carbonica 15x, Bismuthum metallicum 15x, Cadmium metallicum 15x, Calcarea fluorica 15x, Carbo vegetabilis 15x, Carduus marianus 15x Chelidonium majus 15x, Cinchona officinalis 15x, Cobaltum metallicum 15x, Cuprum metallicum 15x, Hydrofluoricum acidum 15x, Iris versicolor 15x, Manganum metallicum 15x, Mercurius vivus 15x, Niccolum metallicum 15x, Platinum metallicum 15x, Plumbum metallicum 15x, Stannum metallicum 15x, Thallium metallicum 15x, Beryllium metallicum 16x, Glycyrrhiza glabra 16x, Osmium metallicum 16x, Strontium carbonicum 16x, Titanium metallicum 16x.

OTC - PURPOSE SECTION

Formulated for associated symptoms such as fatigue, headaches, oversensitivity and sluggish elimination.

INACTIVE INGREDIENT SECTION

Inactive Ingredients: USP Purified Water; USP Gluten-free, non-GMO, organic cane alcohol 20%.

QUESTIONS SECTION

newtonlabs.net – Questions? 800.448.7256

Newton Laboratories, Inc. FDA Est # 1051203 - Conyers, GA 30013

WARNINGS SECTION

WARNINGS: Keep out of reach of children. Do not use if tamper-evident seal is broken or missing. If symptoms worsen or persist for more than a few days, consult a doctor. If pregnant or breast-feeding, ask a doctor before use.

OTC - PREGNANCY OR BREAST FEEDING SECTION

If pregnant or breast-feeding, ask a doctor before use.

OTC - KEEP OUT OF REACH OF CHILDREN SECTION

Keep out of reach of children.